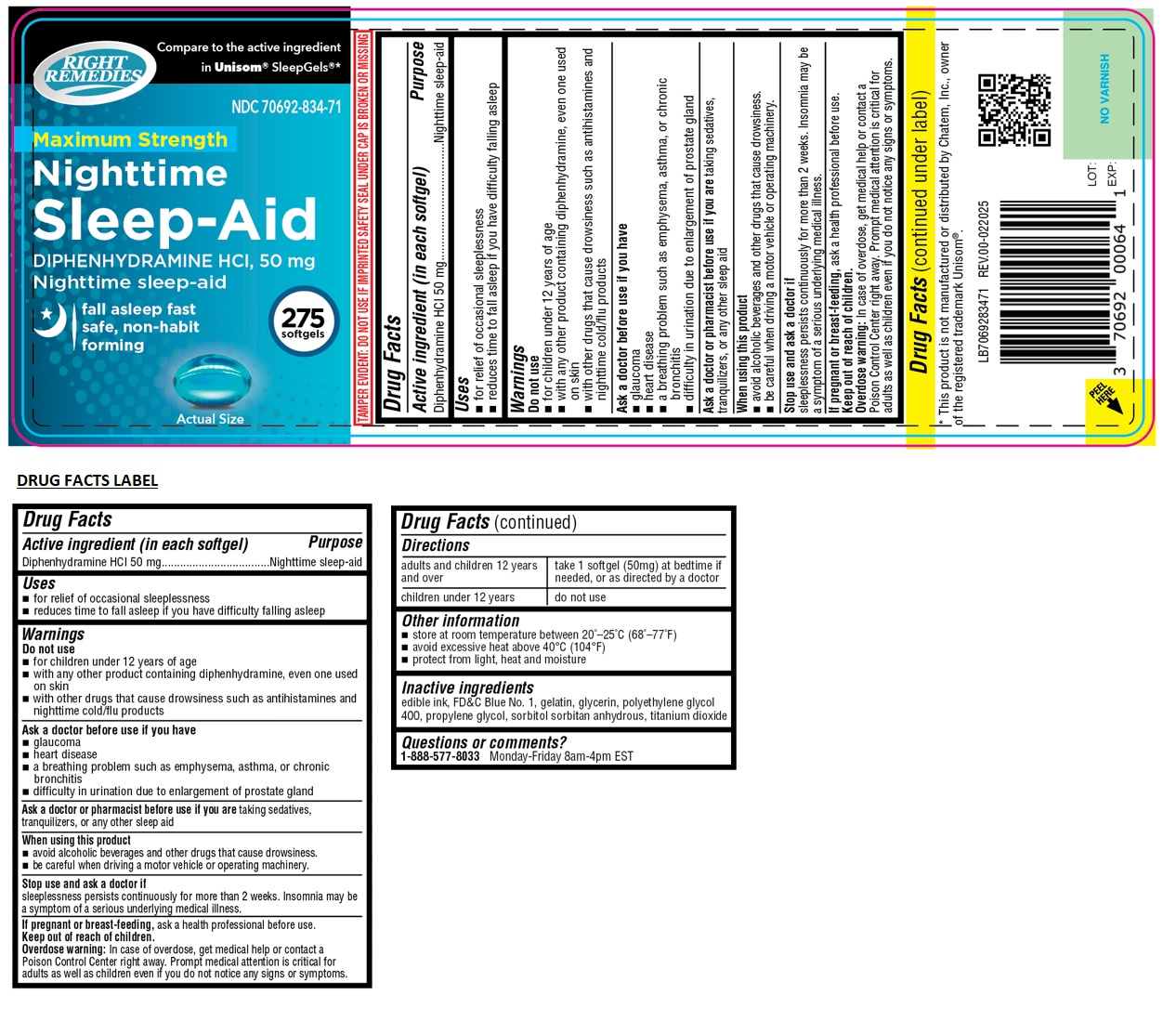 DRUG LABEL: RIGHT REMEDIES Maximum Strength Nighttime Sleep-Aid Softgel
NDC: 70692-834 | Form: CAPSULE, LIQUID FILLED
Manufacturer: Strive Pharmaceuticals Inc.
Category: otc | Type: HUMAN OTC DRUG LABEL
Date: 20250319

ACTIVE INGREDIENTS: DIPHENHYDRAMINE HYDROCHLORIDE 50 mg/1 1
INACTIVE INGREDIENTS: FD&C BLUE NO. 1; GELATIN, UNSPECIFIED; GLYCERIN; POLYETHYLENE GLYCOL 400; PROPYLENE GLYCOL; SORBITOL; SORBITAN; TITANIUM DIOXIDE

RIGHT REMEDIES Maximum Strength Nighttime Sleep-Aid Softgel

Active ingredient (in each softgel)

Diphenhydramine HCl 50 mg

Purpose

Nighttime sleep-aid

Uses

- for relief of occasional sleeplessness
- reduces time to fall alseep if you have difficulty falling asleep

Warnings

Do not use

- for children under 12 years of age
- with any other product containing diphenhydramine, even one used on skin
- with other drugs that cause drowsiness such as antihistamines and nighttime cold/flu products

Ask a doctor before use if you have

- glaucoma
- heart disease
- a breathing problem such as emphysema, asthma, or chronic bronchitis
- difficulty in urination due to an enlargement of prostate gland

Ask a doctor or pharmacist before use if you are taking sedatives, tranquilizers, or any other sleep aid

When using this product

- avoid alcoholic beverages and other drugs that cause drowsiness.
- be careful when driving a motor vehicle or operating machinery.

Stop use and ask a doctor if
sleeplessness persists continuously for more than 2 weeks. Insomnia may be a symptom of a serious underlying medical illness.

If pregnant or breast-feeding, ask a health professional before use.

Keep out of reach of children.
Overdose warning: In case of overdose, get medical help or contact a Poison Control Center right away. Prompt medical attention is critical for adults as well as children even if you do not notice any signs or symptoms.

Directions

adults and children 12 years and over | take 1 softgel (50mg) at bedtime if needed, or as directed by a doctor
children under 12 years | do not use

Other information

- store at room temperature between 20°-25°C (68°-77°F)
- avoid excessive heat above 40°C (104°F)
- protect from light, heat and moisture

Inactive ingredients

edible ink, FD&C Blue No. 1, gelatin, glycerin, polyethylene glycol 400, propylene glycol, sorbitol sorbitan anhydrous, titanium dioxide

Questions or comments?

1-888-577-8033 Monday-Friday 8am-4pm EST

Compare to the active ingredient of Unisom® SleepGels®*

fall asleep fast safe, non-habit forming

TAMPER EVIDENT: DO NOT USE IF IMPRINTED SAFETY SEAL UNDER CAP IS BROKEN OR MISSING

*This product is not manufactured or distributed by Chatem, Inc., owner of the registered trademark Unisom®.

Distributed by: Strive Pharmaceuticals Inc., East Brunswick, NJ 08816

PRODUCT OF INDIA